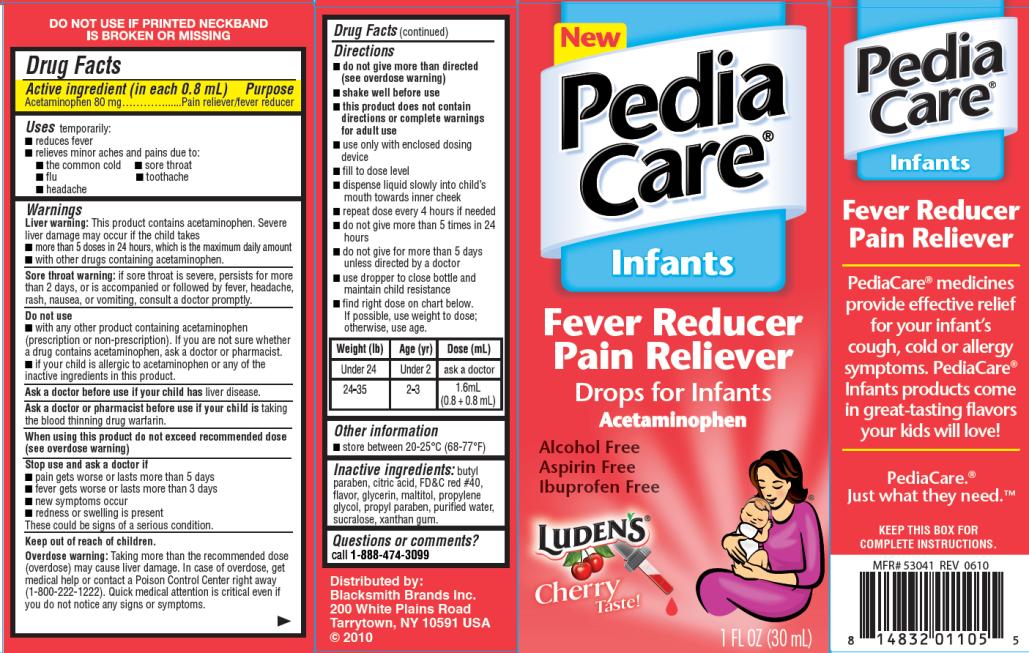 DRUG LABEL: PediaCare Infants Fever Reducer Cherry
NDC: 52183-393 | Form: LIQUID
Manufacturer: Blacksmith Brands, Inc.
Category: otc | Type: HUMAN OTC DRUG LABEL
Date: 20101008

ACTIVE INGREDIENTS: ACETAMINOPHEN 80 mg/0.8 mL
INACTIVE INGREDIENTS: BUTYLPARABEN; CITRIC ACID; FD&C RED NO. 40; GLYCERIN; MALTITOL; PROPYLENE GLYCOL; PROPYLPARABEN; WATER; SUCRALOSE; XANTHAN GUM

PediaCare Infants Fever Reducer Cherry

Drug Facts

Active Ingredients

(in each 0.8 mL)

Acetaminophen 80mg

Purpose

Pain reliever/fever reducer

Uses

temporarily:

- reduces fever
- relieves minor aches and pains due to:
  - the common cold
  - flu
  - sore throat
  - toothache
  - headache

Warnings

Liver warning: This product contains acetaminophen. Severe liver damage may occur if the child takes

- more than 5 doses in 24 hours, which is the maximum daily amount
- with other drugs containing acetaminophen.

Sore throat warning: If sore throat is severe, persists for more than 2 days, or is accompanied or followed by fever, headache, rash, nausea, or vomiting, consult a doctor promptly.

Do not use

- with any other product containing acetaminophen (prescription or non-prescription). If you are not sure whether a drug contains acetaminophen, ask a doctor or pharmacist.
- if your child is allergic to acetaminophen or any of the inactive ingredients in this product.

Ask a doctor before use

if your child has liver disease.

Ask a doctor or pharmacist before use

if your child is taking the blood thinning drug warfarin.

When using this product

do not exceed recommended dose.

(see overdose warning)

Stop use and ask a doctor if

- pain gets worse or lasts more than 5 days
- fever gets worse or lasts more than 3 days
- new symptoms occur
- redness or swelling is present

These could be signs of a serious condition.

Overdose warning:

Taking more than the recommended dose (overdose) may cause liver damage. In case of overdose, get medical help or contact a Poison Control Center right away (1-800-222-1222). Quick medical attention is critical even if you do not notice any signs or symptoms.

Directions

- do not give more than directed (see overdose warning)
- shake well before use
- this product does not contain directions or complete warnings for adult use
- use only with enclosed dosing device
- fill to dose level
- dispense liquid slowly into child’s mouth towards inner cheek
- repeat dose every 4 hours if needed
- do not give more than 5 times in 24 hours
- do not give for more than 5 days unless directed by a doctor
- use dropper to close bottle and maintain child resistance
- find right dose on chart below. If possible, use weight to dose; otherwise, use age.

Weight (lb) | Age (yr) | Dose (mL)
Under 24 | Under 2 | ask a doctor
24-35 | 2-3 | 1.6 mL (0.8 + 0.8 mL)

Other information

store between 20-25ºC (68-77ºF)

Inactive ingredients:

butyl paraben, citric acid, FD&C Red #40, flavor, glycerin, maltitol, propylene glycol, propyl paraben, purified water, sucralose, xanthan gum.

Questions or comments?

call 1-888-474-3099

Distributed by:
Blacksmith Brands Inc.
200 White Plains Road
Tarrytown, NY 10591 USA
© 2010

PRINCIPAL DISPLAY PANEL

NEW PediaCare® Infants
Fever Reducer Pain Reliever
Ludens® Cherry Taste!
1 FL OZ (30 mL)